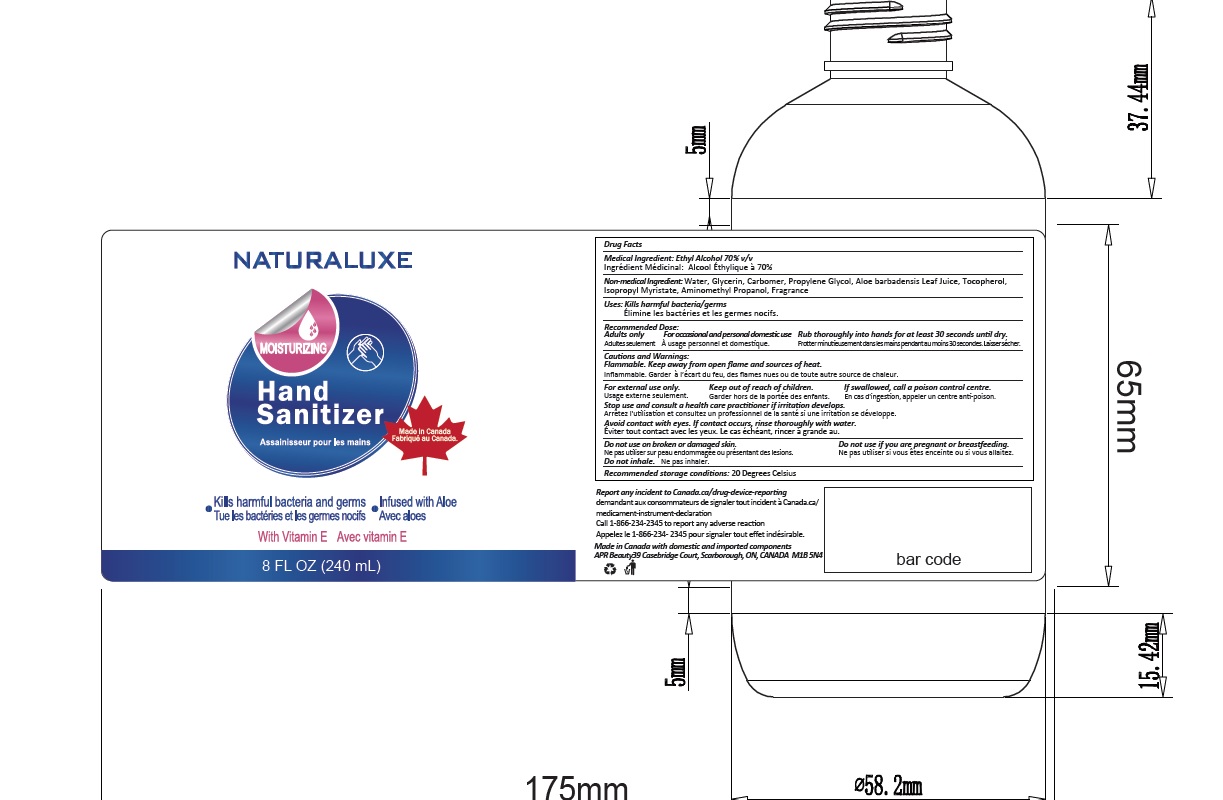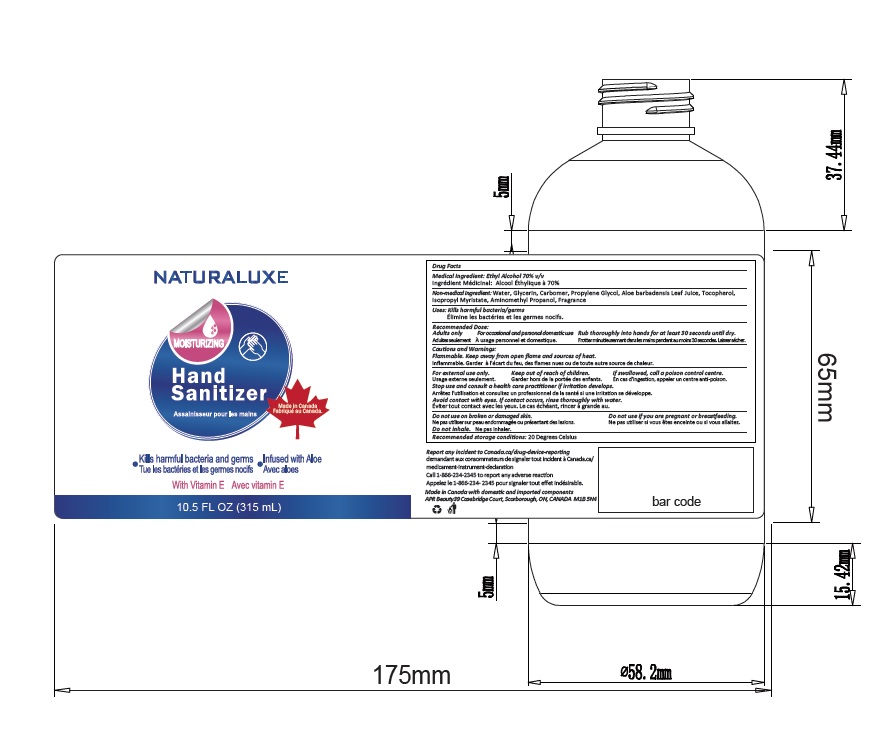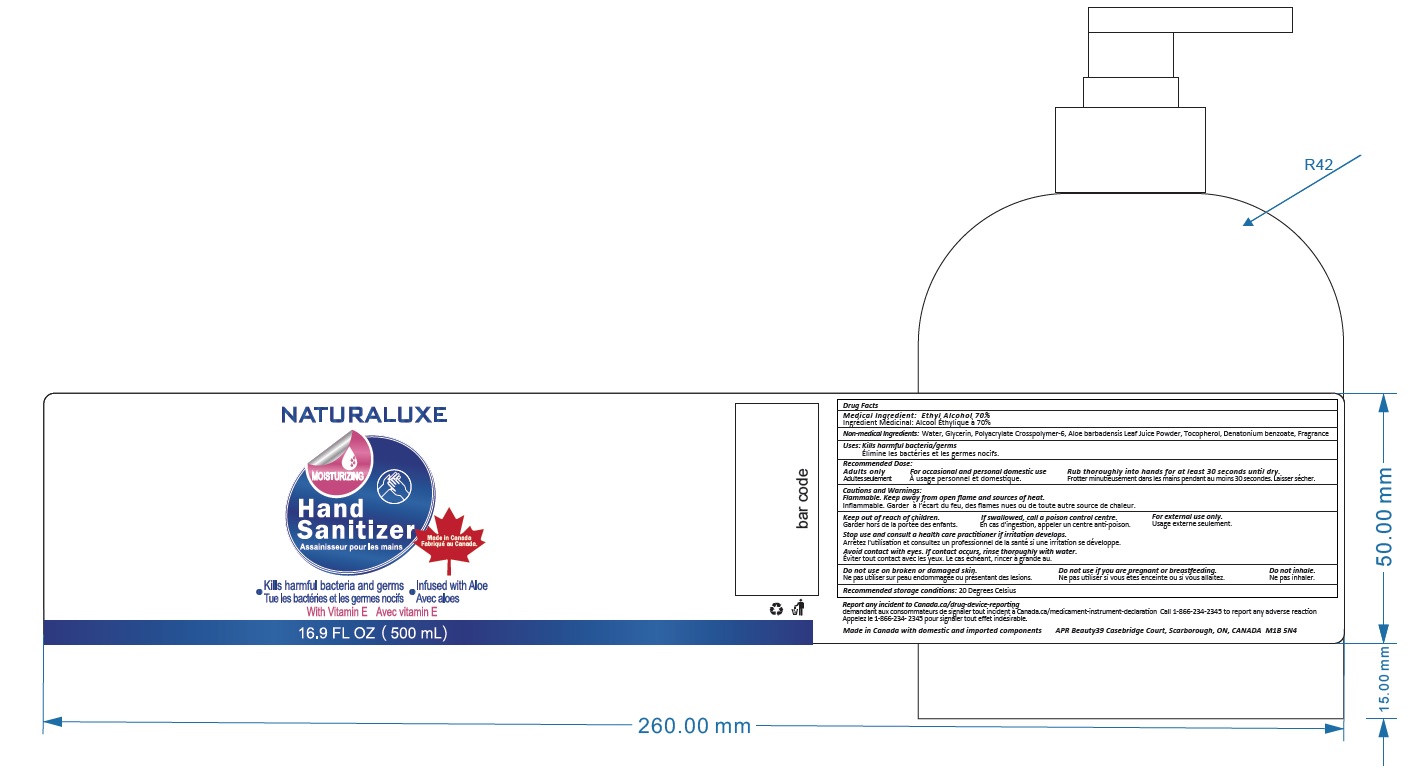 DRUG LABEL: SeaLuxe Hand Sanitizer
NDC: 79959-001 | Form: GEL
Manufacturer: APR Beauty Group Inc.
Category: otc | Type: HUMAN OTC DRUG LABEL
Date: 20200831

ACTIVE INGREDIENTS: ALCOHOL 70 mL/100 mL
INACTIVE INGREDIENTS: ISOPROPYL MYRISTATE; WATER; PROPYLENE GLYCOL; CARBOMER INTERPOLYMER TYPE A (ALLYL SUCROSE CROSSLINKED); GLYCERIN; ALOE VERA LEAF; AMINOMETHYLPROPANOL; TOCOPHEROL

Naturaluxe Hand Sanitizer

Drug Facts

Active Ingredient

Ethyl Alcohol, 70% w/w

Purpose

Antiseptic

Uses

Kills harmful bacteria/germs

Warnings

Flammable, keep away from open flame and sources of heat.

WHEN USING

For occasional and personal domestic use.

Stop use and consult a health care practitioner if irritation develops.

Avoid contact with eyes.

If contact occurs, rinse thoroughly with water.

KEEP OUT OF REACH OF CHILDREN

If swallowed, call a posion control centre.

Directions

Rub thoroughly into hands for at least 30 seconds until dry.

For children 2 years and over supervise when product is used

Other Information

Recommended storage conditions:

20 Degress Celsius

Inactive Ingredients

Aloe barbadensis leaf juice, Aminomethyl Propanol, Glycerin , Propylene Glycol, Water, Isopropyl Myristate,Carbomer